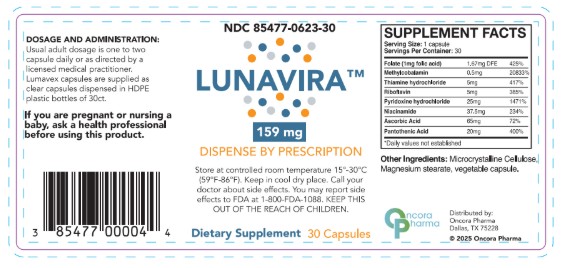 DRUG LABEL: Lunavira
NDC: 85477-623 | Form: CAPSULE
Manufacturer: Oncora Pharma, LLC
Category: prescription | Type: HUMAN PRESCRIPTION DRUG LABEL
Date: 20251231

ACTIVE INGREDIENTS: THIAMINE HYDROCHLORIDE 5 mg/1 1; NIACINAMIDE 35.7 mg/1 1; PYRIDOXINE HYDROCHLORIDE 25 mg/1 1; ASCORBIC ACID 65 mg/1 1; PANTOTHENIC ACID 20 mg/1 1; RIBOFLAVIN 5 mg/1 1; FOLIC ACID 1 mg/1 1; METHYLCOBALAMIN 0.5 mg/1 1
INACTIVE INGREDIENTS: CELLULOSE, MICROCRYSTALLINE; MAGNESIUM STEARATE

DESCRIPTION

Lunavira is a prescription multivitamin/multimineral dietary supplement with 1mg Folic Acid.

WARNINGS

WARNING If you are pregnant or nursing, ask a health care professional before using this product. Keep this product out of the reach of children.

ADVERSE REACTIONS

Call your doctor about side effects. You may report side effects to the FDA at 1-800-FDA-1088.

DOSAGE AND ADMINISTRATION

Usual adult dosage is one to two capsule daily or as directed by a licensed medical practitioner.

HOW SUPPLIED

Lunavira capsules are supplied as clear capsules dispensed in HDPE plastic bottles of 30 count (85477-623-30).

STORAGE AND HANDLING

STORAGE: Store at controlled room temperature 15°-30° C (59°-86° F). Keep in a cool dry place.

MADE IN USA
Distributed by:
888-321-2821
Oncora Pharma
Dallas, TX 75161

OTHER SAFETY INFORMATION

KEEP THIS AND ALL MEDICATIONS OUT OF THE REACH OF CHILDREN